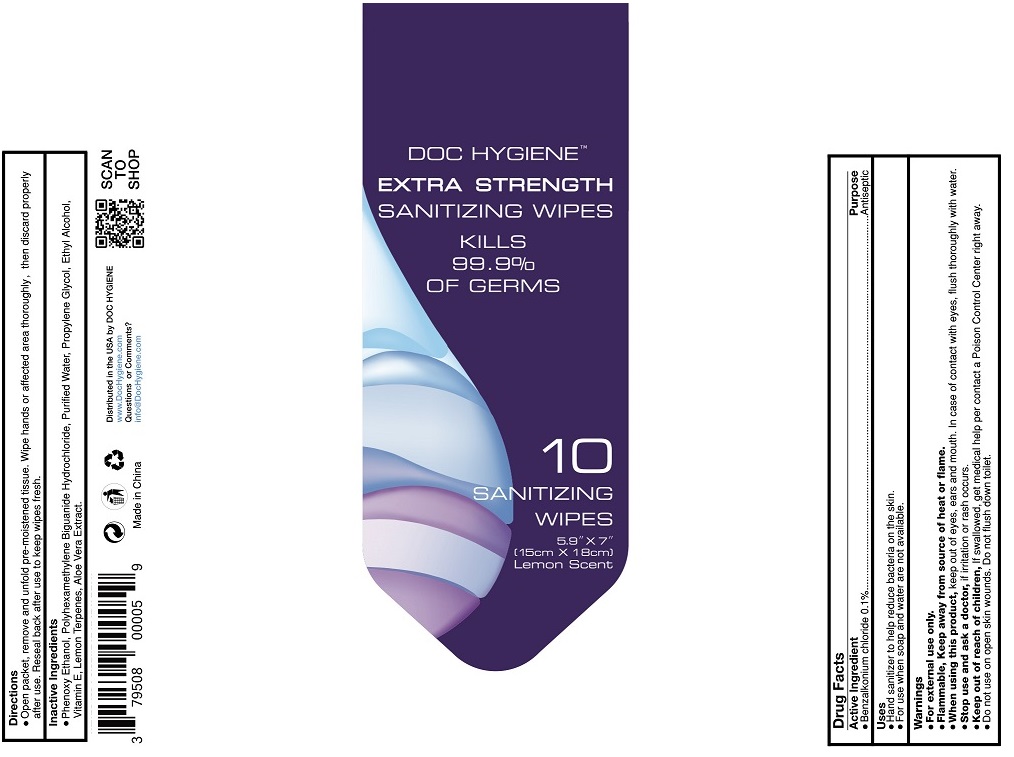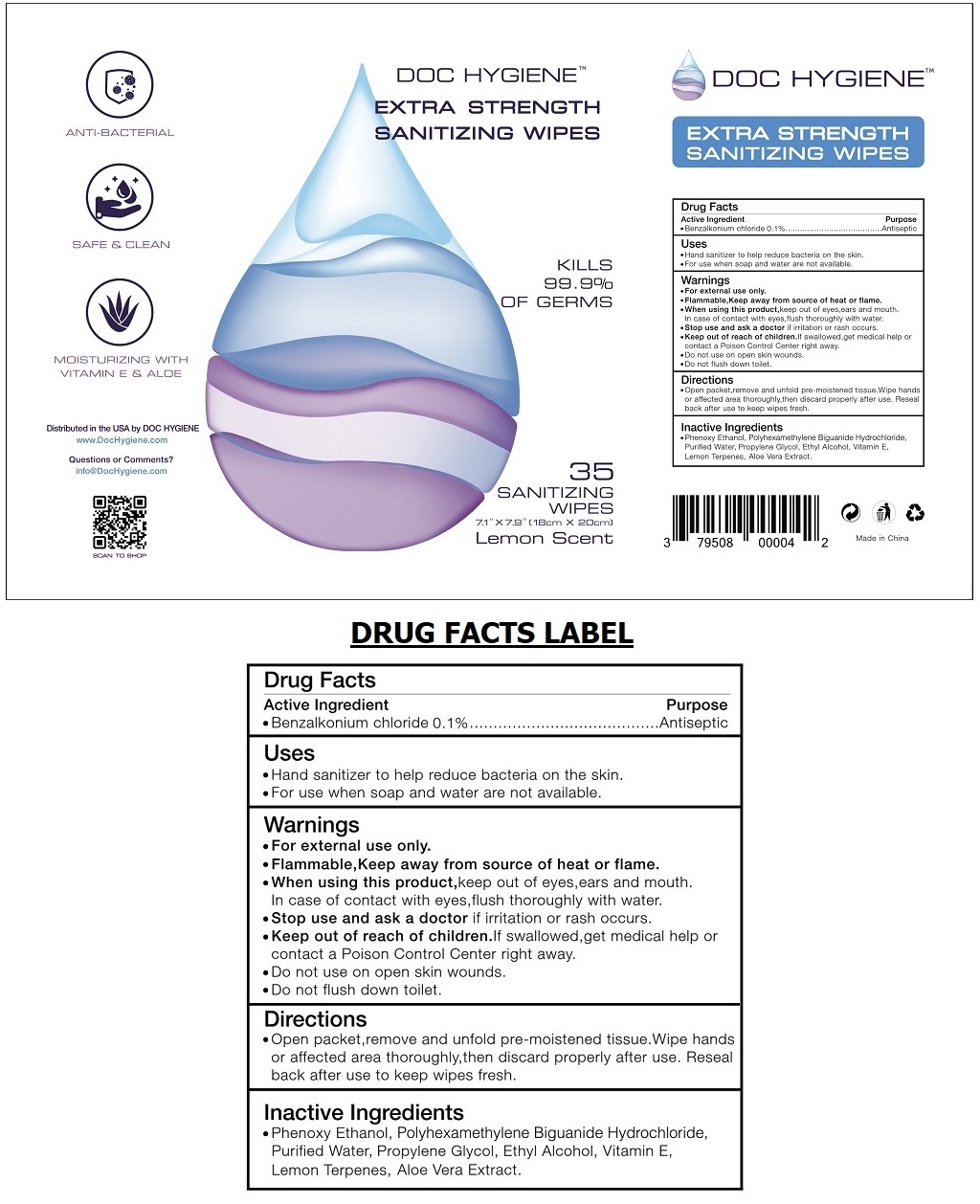 DRUG LABEL: DOC HYGIENE EXTRA STRENGTH SANITIZING WIPES
NDC: 79508-020 | Form: CLOTH
Manufacturer: Blue Flame Medical Llc
Category: otc | Type: HUMAN OTC DRUG LABEL
Date: 20200825

ACTIVE INGREDIENTS: BENZALKONIUM CHLORIDE 0.1 g/100 g
INACTIVE INGREDIENTS: PHENOXYETHANOL; POLIHEXANIDE HYDROCHLORIDE; WATER; PROPYLENE GLYCOL; ALCOHOL; .ALPHA.-TOCOPHEROL; LEMON TERPENES; ALOE VERA LEAF

DOC HYGIENE™ EXTRA STRENGTH SANITIZING WIPES

Active Ingredient

• Benzalkonium chloride 0.1%

Purpose

Antiseptic

Uses

• Hand sanitizer to help reduce bacteria on the skin.

• For use when soap and water are not available.

Warnings

• For external use only.

• Flammable, Keep away from source of heat or flame.

• When using this product, keep out of eyes, ears, and mouth.

In case of contact with eyes, flush thoroughly with water.

• Stop use and ask a doctor if irritation or rash occurs.

• Do not use on open skin wounds.

• Do not flush down toilet.

• Keep out of reach of children. If swallowed, get medical help or contact a Poison Control Center right away.

Directions

• Open packet, remove and unfold pre-moistened tissue. Wipe hands or affected area thoroughly, then discard properly after use. Reseal back after use to keep wipes fresh.

Inactive Ingredients

• Phenoxy Ethanol, Polyhexamethylene Biguanide Hydrochloride, Purified Water, Propylene Glycol, Ethyl Alcohol, Vitamin E, Lemon Terpenes, Aloe Vera Extract.

KILLS 99.9% OF GERMS

Lemon Scent

ANTI-BACTERIAL

SAFE & CLEAN

MOISTURIZING WITH VITAMIN E & ALOE

Distributed in the USA by DOC HYGIENE

www.DocHygiene.com

Questions or Comments?

info@DocHygiene.com

Made in China